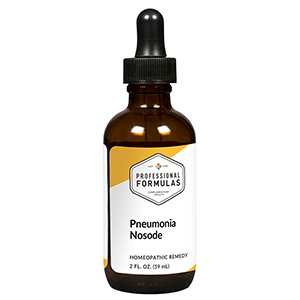 DRUG LABEL: Pneumonia Nosode
NDC: 63083-4016 | Form: LIQUID
Manufacturer: Professional Complementary Health Formulas
Category: homeopathic | Type: HUMAN OTC DRUG LABEL
Date: 20190815

ACTIVE INGREDIENTS: HUMAN ADENOVIRUS B SEROTYPE 3 30 [hp_X]/59 mL; CHLAMYDIA TRACHOMATIS 30 [hp_X]/59 mL; CHLAMYDOPHILA PSITTACI 30 [hp_X]/59 mL; COCCIDIOIDES IMMITIS WHOLE 30 [hp_X]/59 mL; COXSACKIEVIRUS A21 30 [hp_X]/59 mL; HAEMOPHILUS INFLUENZAE 30 [hp_X]/59 mL; STREPTOCOCCUS VIRIDANS GROUP 30 [hp_X]/59 mL; HISTOPLASMA CAPSULATUM 30 [hp_X]/59 mL; INFLUENZA A VIRUS A/VICTORIA/2454/2019 IVR-207 (H1N1) ANTIGEN (FORMALDEHYDE INACTIVATED) 30 [hp_X]/59 mL; KLEBSIELLA PNEUMONIAE 30 [hp_X]/59 mL; MYCOBACTERIUM TUBERCULOSIS 30 [hp_X]/59 mL; MYCOPLASMA PNEUMONIAE 30 [hp_X]/59 mL; STREPTOCOCCUS PYOGENES 30 [hp_X]/59 mL; HUMAN RESPIRATORY SYNCYTIAL VIRUS 30 [hp_X]/59 mL; COXIELLA BURNETII 30 [hp_X]/59 mL; RICKETTSIA RICKETTSII 30 [hp_X]/59 mL; STAPHYLOCOCCUS AUREUS 30 [hp_X]/59 mL
INACTIVE INGREDIENTS: ALCOHOL; WATER

N16

ACTIVE INGREDIENTS

all the following at 30X, 60X:
Adenovirus
Chlamydia pneumoniae
Chlamydia psittaci
Chlamydia trachomatis
Coccidioides immitis
Coxsackievirus
Haemophilus influenzae
Hemolytic streptococcus
Histoplasma capsulatum
Influenzinum
Klebsiella pneumoniae
Mycobacterium tuberculosis
Mycoplasma pneumoniae
Pneumococcinum
Respiratory syncytial virus (RSV)
Rhinopneumonitis
Rickettsia burnetii
Rickettsia rickettsii
Staphylococcus

QUESTIONS

Professional Formulas

PO Box 2034 Lake Oswego, OR 97035

INDICATIONS

For the temporary relief of cough, congestion, chills, difficulty breathing, or feelings of discomfort or uneasiness.*

PURPOSE

*Claims based on traditional homeopathic practice, not accepted medical evidence. Not FDA evaluated.

WARNINGS

Persistent symptoms may be a sign of a serious condition. Consult a doctor promptly if symptoms persist or are accompanied by a fever. Keep out of the reach of children. In case of overdose, get medical help or contact a poison control center right away. If pregnant or breastfeeding, ask a healthcare professional before use.

Keep out of the reach of children.

PREGNANCY OR BREAST FEEDING

If pregnant or breastfeeding, ask a healthcare professional before use.

DIRECTIONS

Place drops under tongue 30 minutes before/after meals. Adults and children 12 years and over: Take 10 to 15 drops once weekly or monthly. If mild symptoms are present, take 10 drops up to 3 times per day. Consult a physician for use in children under 12 years of age.

OTHER INFORMATION

Tamper resistant. If seal is broken, do not use. After opening, close container tightly and store at room temperature away from heat.

INACTIVE INGREDIENTS

20% ethanol, purified water.

LABEL

Est 1985

Professional Formulas

Complementary Health

Pneumonia Nosode

Homeopathic Remedy

2 FL. OZ. (59 mL)